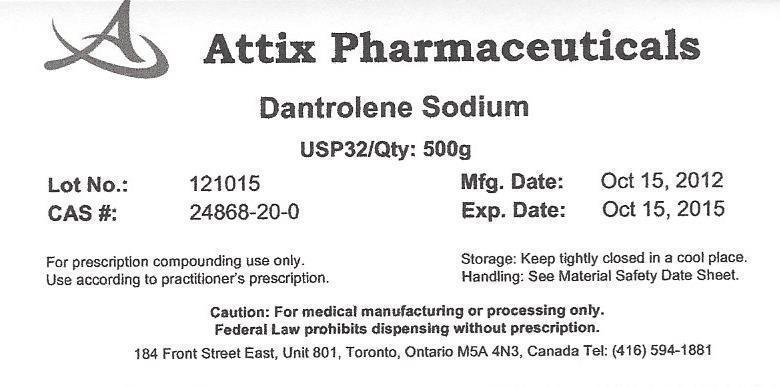 DRUG LABEL: Dantrolene Sodium
NDC: 75839-229 | Form: POWDER
Manufacturer: Attix Pharmaceuticals
Category: other | Type: BULK INGREDIENT
Date: 20140106

ACTIVE INGREDIENTS: DANTROLENE SODIUM 500 g/500 g

Dantrolene Sodium